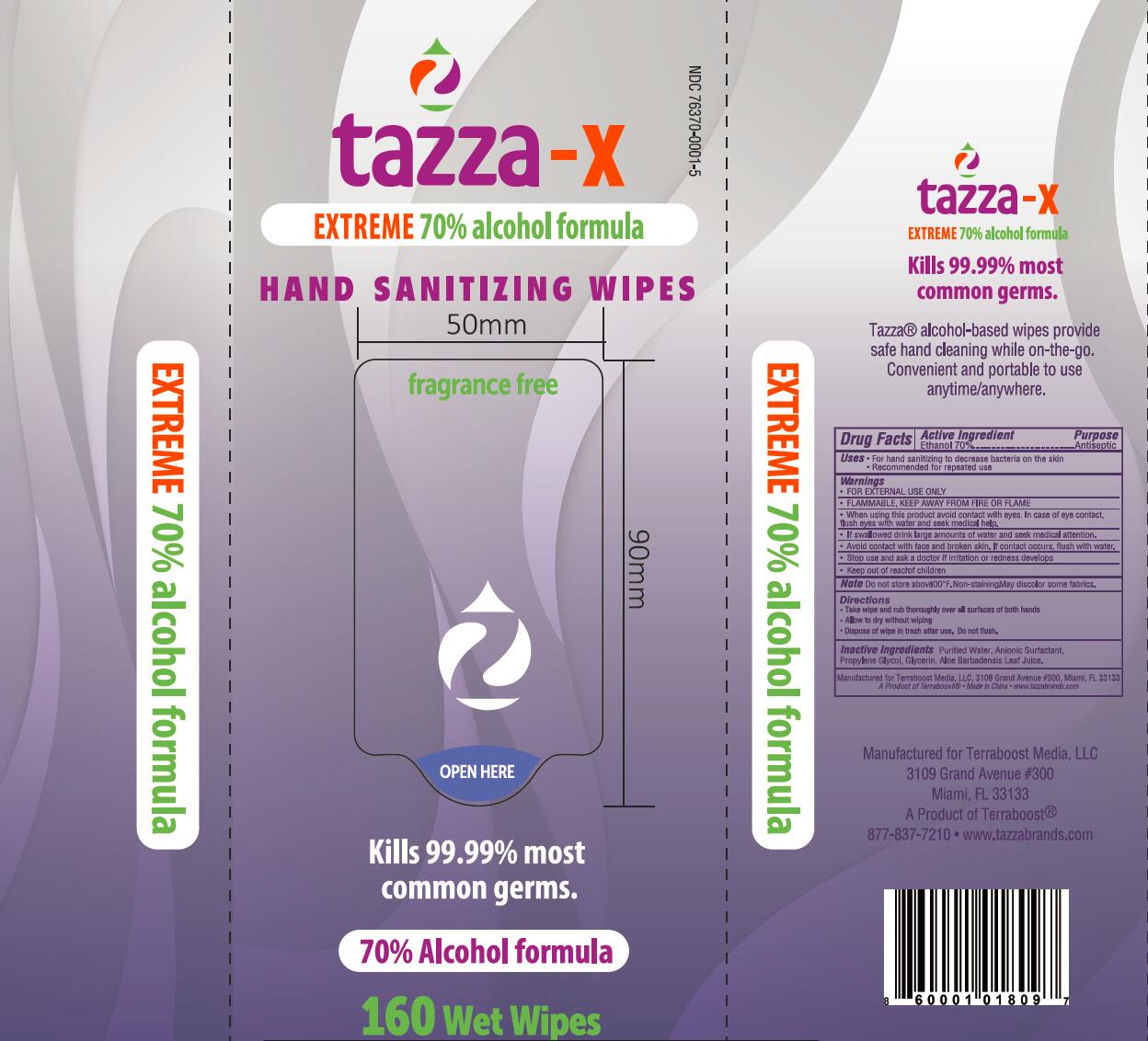 DRUG LABEL: Wet Wipes
NDC: 69821-003 | Form: SWAB
Manufacturer: Zhejiang Qimei Commodity Co.,Ltd.
Category: otc | Type: HUMAN OTC DRUG LABEL
Date: 20221102

ACTIVE INGREDIENTS: ALCOHOL 70 g/100 g
INACTIVE INGREDIENTS: GLYCERIN; PROPYLENE GLYCOL; DECYL GLUCOSIDE; ALOE VERA LEAF; WATER

69821-003 70% Alcohol Wet Wipes

Active ingredient

Ethyl Alcohol 70%

Purpose

Antiseptic

Uses

●For hand sanitizing to decrease bacteria on the skin
●Recommended for repeated use

Warnings

. FOR EXTERNAL USE ONLY
. FLAMMABL E, KEEP AWAY FROM FIRE OR FL AME
●When using this product avoid contact with eyes. In case of eye contact,
flush eyes with water and seek medical help.
●If swallowed drink large amounts of water and seek medical attention.
●Avoid contact with face and broken skin. If contact occurs, flush with water.
●Stop use and ask a doctor if rritation or redness develops
Note Do not store above00°F. Non-stainingMay discolor some fabrics.

Keep out of reach of children

Directions

●Take wipe and rub thoroughly over all surfaces of both hands
●Allow to dry without wiping
●Dispose of wipe in trash after use. Do not flush.

INACTIVE INGREDIENT

Purfied Water, Anionic Surfactant,
Propylene Glycol, Glycerin, Aloe Barbadensis Leaf Juice.